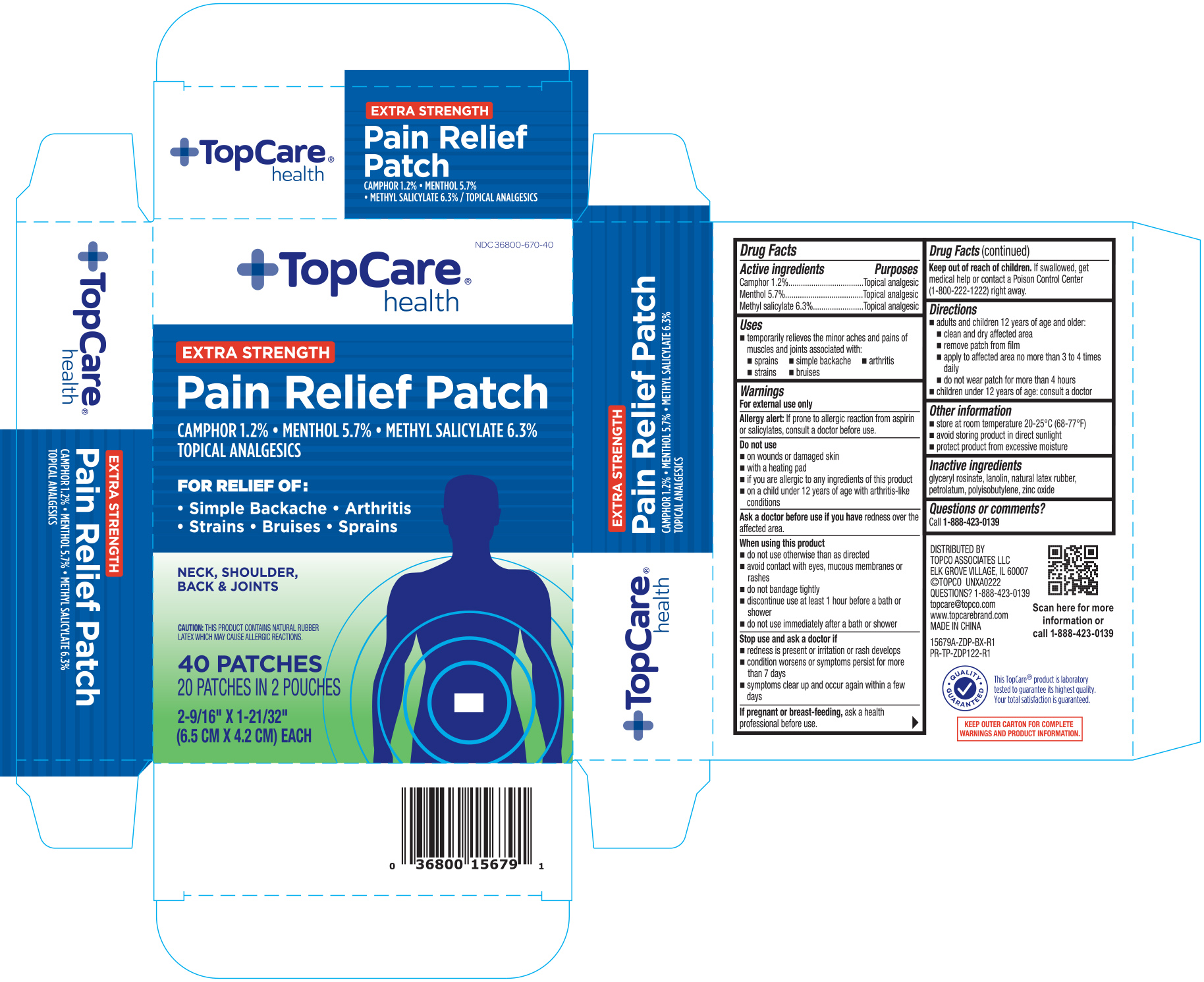 DRUG LABEL: TopCare Health Pain Relief
NDC: 36800-670 | Form: PATCH
Manufacturer: Topco Associates LLC
Category: otc | Type: HUMAN OTC DRUG LABEL
Date: 20251030

ACTIVE INGREDIENTS: CAMPHOR (SYNTHETIC) 0.012 mg/1 g; MENTHOL 0.057 mg/1 g; METHYL SALICYLATE 0.063 mg/1 g
INACTIVE INGREDIENTS: GLYCERYL ROSINATE; NATURAL LATEX RUBBER; PETROLATUM; ZINC OXIDE; POLYISOBUTYLENE (1000 MW); LANOLIN

TopCare Health Extra Strength Pain Relief Patch 40 ct 15679A

Active ingredients Purposes

Camphor 1.2%.......................................Topical analgesic

Menthol 5.7%.........................................Topical analgesic

Methyl salicylate 6.3%............................Topical analgesic

Uses

- temporarily relieves the minor aches and pains of muscles and joints associated with:
- sprains
- simple backache
- arthritis
- strains
- bruises

Warnings

For external use only

Allergy alert: If prone to allergic reaction from aspirin or salicylates, consult a doctor before use.

Do not use

- on wounds or damaged skin
- with a heating pad
- if you are allergic to any ingredients of this product
- on a child under 12 years of age with arthritis-like conditions

Ask a doctor before use if you have redness over the affected area.

When using this product

- do not use otherwise than as directed
- avoid contact with eyes, mucous membranes or rashes
- do not bandage tightly
- discontinue use at least 1 hour before a bath or shower
- do not use immediately after a bath or shower

Stop use and ask a doctor if

- redness is present or irritation or rash develops
- condition worsens or symptoms persist for more than 7 days
- symptoms clear up and occur again within a few days

PREGNANCY OR BREAST FEEDING

If pregnant or breast-feeding, ask a health professional before use.

Keep out of reach of children. If swallowed, get medical help or contact a Poison Control Center (1-800-222-1222) right away.

Directions

- adults and children 12 years of age and older:
- clean and dry affected area
- remove patch from film
- apply to affected area no more than 3 to 4 times daily
- do not wear patch for more than 4 hours
- children under 12 years of age: consult a doctor

Other information

- store at room temperature 20-25°C (68-77°F)
- avoid storing product in direct sunlight
- protect product from excessive moisture

Inactive ingredients

glyceryl rosinate, lanolin, natural latex rubber, petrolatum, polyisobutylene, zinc oxide

DOSAGE AND ADMINISTRATION

Distributed by:

Topco Associates LLC

Elk Grove IL 60007

Made in China